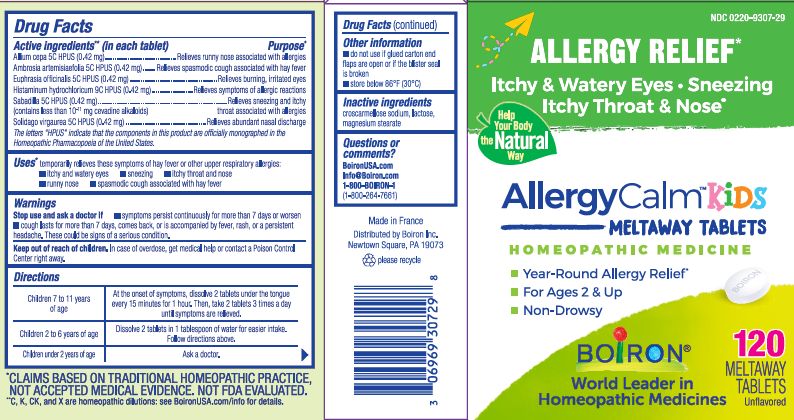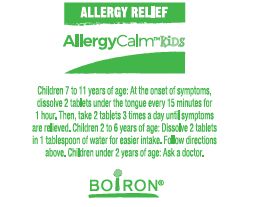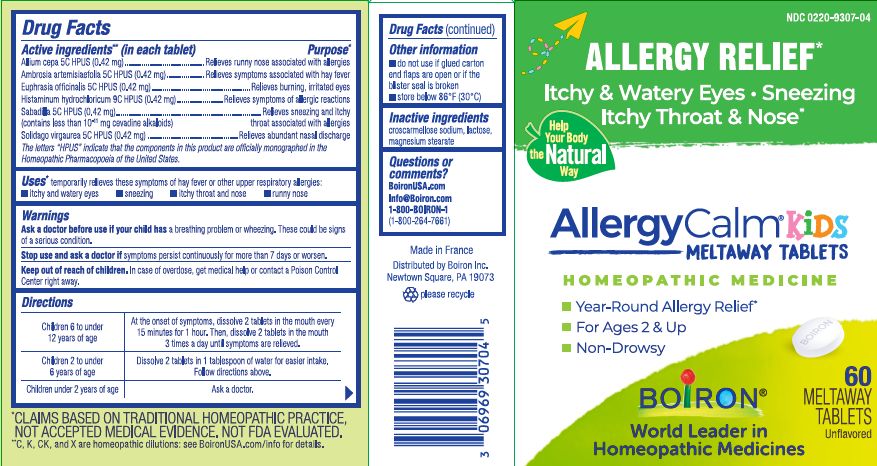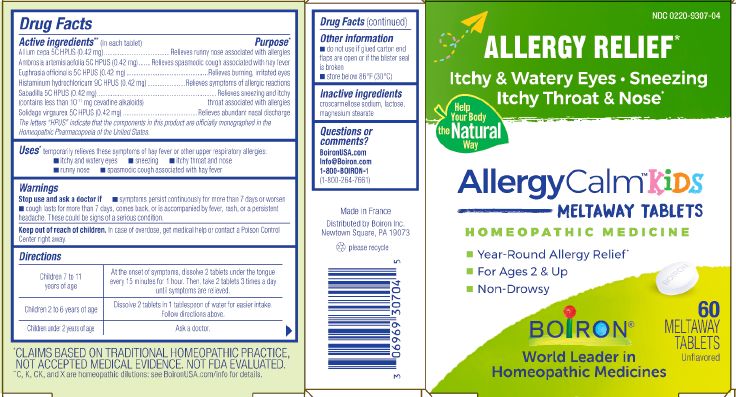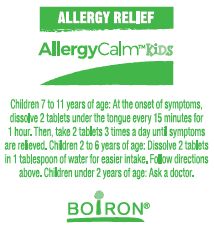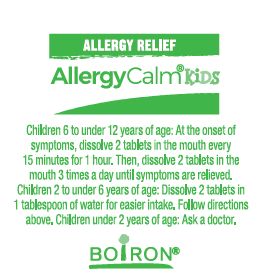 DRUG LABEL: AllergyCalm
NDC: 0220-9307 | Form: TABLET
Manufacturer: Boiron
Category: homeopathic | Type: HUMAN OTC DRUG LABEL
Date: 20250809

ACTIVE INGREDIENTS: EUPHRASIA STRICTA 5 [hp_C]/1 1; HISTAMINE DIHYDROCHLORIDE 9 [hp_C]/1 1; SCHOENOCAULON OFFICINALE SEED 5 [hp_C]/1 1; ONION 5 [hp_C]/1 1; SOLIDAGO VIRGAUREA FLOWERING TOP 5 [hp_C]/1 1; AMBROSIA ARTEMISIIFOLIA 5 [hp_C]/1 1
INACTIVE INGREDIENTS: MAGNESIUM STEARATE; CROSCARMELLOSE SODIUM; LACTOSE, UNSPECIFIED FORM

AllergyCalm Kids Tablets

Active ingredients** (in each tablet)

Allium cepa 5C HPUS (0.42 mg)

Ambrosia artemisiaefolia 5C HPUS (0.42 mg)

Euphrasia officinalis 5C HPUS (0.42 mg)

Histaminum hydrochloricum 9C HPUS (0.42 mg)

Sabadilla 5C HPUS (0.42 mg) (contains less than 10^-11 mg cevadine alkaloids)

Solidago vigaurea 5C HPUS (0.42 mg)

The letters "HPUS" indicate that the components in this product are officially monographed in the Homeopathic Pharmacopoeia of the United States.

Purpose*

Allium cepa 5C HPUS (0.42 mg) ... Relieves runny nose associated with allergies

Ambrosia artemisiaefolia 5C HPUS (0.42 mg) ... Relieves symptoms associated with hay fever

Euphrasia officinalis 5C HPUS (0.42 mg) ... Relieves burning, irritated eyes

Histaminum hydrochloricum 9C HPUS (0.42 mg) ... Relieves symptoms of allergic reactions

Sabadilla 5C HPUS (0.42 mg) ... Relieves sneezing and itchy throat associated with allergies

Solidago vigaurea 5C HPUS (0.42 mg) ... Relieves abundant nasal discharge

Uses*

temporarily relieves these symptoms of hay fever or other upper respiratory allergies:

itchy and watery eyes
sneezing
itchy throat and nose
runny nose

Warnings

Ask a doctor before use if your child has a breathing problem or wheezing. These could be signs of a serious condition.

Stop use and ask a doctor if symptoms persist continuously for more than 7 days or worsen.

Keep out of reach of children. In case of overdose, get medical help or contact a Poison Control Center right away.

Directions

Children 6 to 12 years of age - At the onset of symptoms, dissolve 2 tablets in the mouth every 15 minutes for 1 hour. Then, dissolve 2 tablets in the mouth 3 times a day until symptoms are relieved.

Children 2 to 6 years of age - Dissolve 2 tablets in 1 tablespoon of water for easier intake. Follow directions above.

Children under 2 years of age - Ask a doctor.

Other information

- do not use if glued carton end flaps are open or if the blister seal is broken
- store below 86° F (30° C)

INACTIVE INGREDIENT

croscarmellose sodium, lactose, magnesium stearate

QUESTIONS

BoironUSA.com

Info@Boiron.com

1-800-BOIRON-1

(1-800-264-7661)

Made in France

Distributed by Boiron, Inc.

Newtown Square, PA 19073

60 Meltaway tablets unflavored

120 Meltaway tablets unflavored

Allergy Relief*

Itchy & Watery Eyes Sneezing Itchy Throat & Nose*

Year-Round Allergy Relief*

Non-Drowsy

*CLAIMS BASED ON TRADITIONAL HOMEOPATHIC PRACTICE NOT ACCEPTED MEDICAL EVIDENCE. NOT FDA EVALUATED.
**C,K,CK, and X are homeopathic dilutions: see BoironUSA.com/info for details.